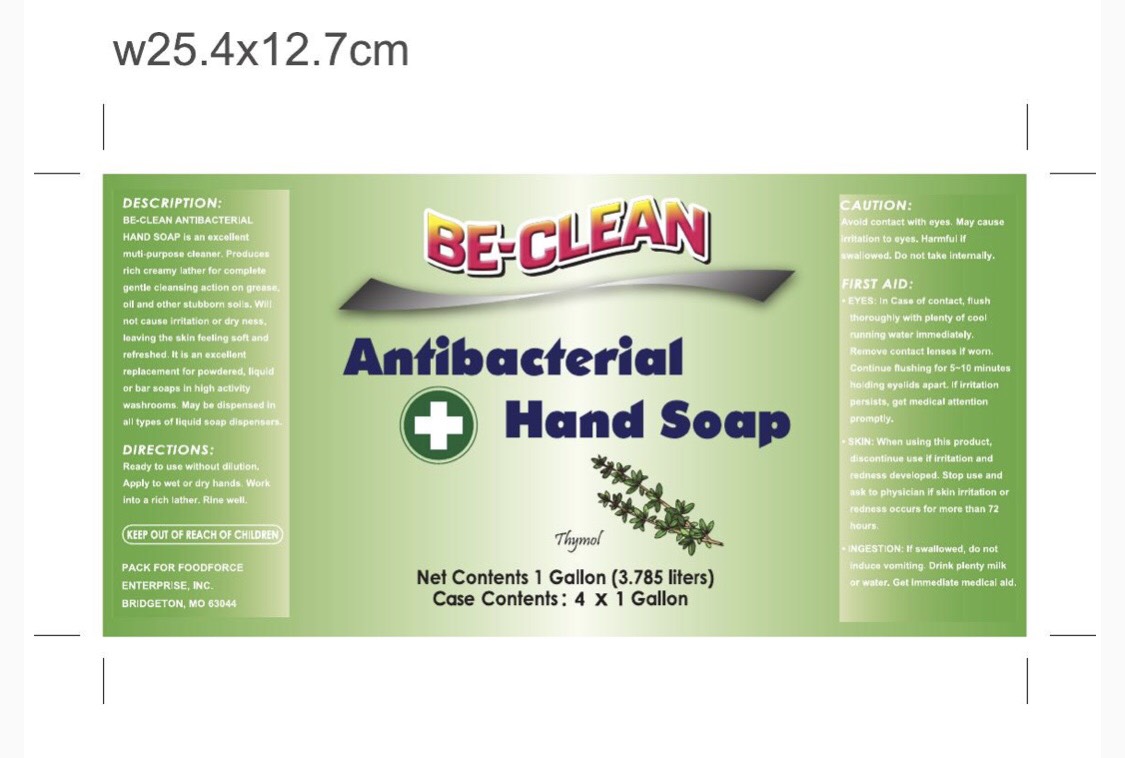 DRUG LABEL: BE CLEAN
NDC: 80590-002 | Form: LIQUID
Manufacturer: CLEANFORCE LLC
Category: otc | Type: HUMAN OTC DRUG LABEL
Date: 20201014

ACTIVE INGREDIENTS: O-CYMEN-5-OL 0.085 mg/100 mg; THYMOL 1.35 mg/100 mg
INACTIVE INGREDIENTS: SODIUM BENZOATE; POTASSIUM CHLORIDE; WATER; LAURAMIDOPROPYL BETAINE; COCO DIETHANOLAMIDE; PALMITIC ACID; EDETATE DISODIUM; GLYCOL DISTEARATE; LAURIC ACID; 2-(2-(2-(2-PHENOXYETHOXY)ETHOXY)ETHOXY)ETHANOL; FRAGRANCE CLEAN ORC0600327; SODIUM LAURETH SULFATE; GLYCERIN; SODIUM LACTATE; MYRISTIC ACID

BE CLEAN ANTIBACTERIAL HAND SOAP

DESCRIPTION

BE-CLEAN ANTIBACTERIAL HAND SOAP is an excellent multi purpose cleaner. Produces rich creamy lather for complete gentle cleansing action on grease, oil and other stubborn soils. Will not cause irritation or dryness, leaving the skin feeling soft and refreshed. It is an excellent replacement for powdered, liquid or bar soaps in high activity washrooms. May be dispensed in all types of liquid soap dispensers.

DIRECTIONS:

Ready to use without dilution. Apply to wet or dry hands. Work into a rich lather. Rinse well.

DIRECTIONS:

Apply to wet or dry hands. Work into a rich lather. Rinse well.

Liquid

Apply to wet or dry hands. Work into rich lather. Rinse well.

ACTIVE INGREDIENT

Thymol

CAUTION:

Avoid contact with eyes. May cause irritation to eyes. Harmful if swallowed. Do not take internally.

KEEP OUT OF REACH OF CHILDREN

Warning

KEEP OUT OF REACH OF CHILDREN

FIRST AID:

* EYES: In Case of contact, flush thoroughly with plenty of cool running water immediately. Remove contact lenses if worn. Continue flushing for 5-10 minutes holding eyelids apart. If irritation persists, get medical attention promptly.

* SKIN: When using this product discontinue use if irritation and redness developed. Stop use and ask to physician if skin irritation or redness occurs for more than 72 hours.

* INGESTION: If swallowed. do not induce vomiting. Drink plenty milk or water. Get Immediate medical aid.

STATEMENT OF IDENTITY

PACK FOR FOODFORCE ENTERPRISE, INC.

BRIDGETON, MO 63044

Inactive Ingredients

Water 72.5%

Palmitic Acid 10%

Lauryl Ether Sulfate 4%

Myristic Acid 2.5%

Lauric Acid 2.5%

Glycol Distearate 2%

Potassium Chloride 1.25%

Glycerin 1.25%

Lauramidopropyl Betaine 1.25%

Sodium Lactate 0.8%

Coco Diethanolamide 0.8%

Phenoxyethanol (Preservative) 0.625%

Fragrance 0.375%

Sodium Benzoate 0.085%

Edetate Disodium 0.085%

Purpose

It is a disinfecting and sanitizing replacement for powdered, bar or liquid soaps in high activity washrooms.